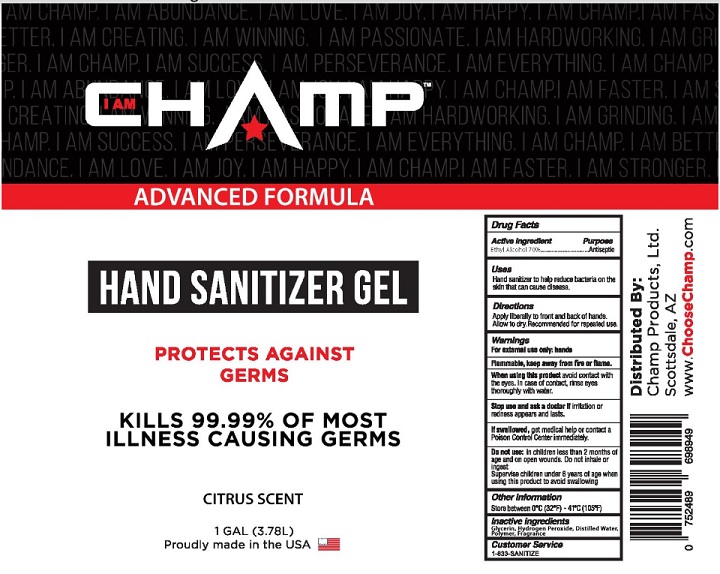 DRUG LABEL: Champ
NDC: 78658-001 | Form: GEL
Manufacturer: Champ Products, Ltd
Category: otc | Type: HUMAN OTC DRUG LABEL
Date: 20200508

ACTIVE INGREDIENTS: ALCOHOL 70 mL/100 mL
INACTIVE INGREDIENTS: WATER; HYDROGEN PEROXIDE; GLYCERIN; GUARAPROLOSE (3500 MPA.S AT 1%); FRAGRANCE LAVENDER & CHIA F-153480

Active Ingredient

Ethyl Alcohol 70%

Purpose

Antiseptic

Uses

Hand Sanitizer to help reduce bacteria that potentially can cause disease.

Directions

Apply liberally to front and back of hands. Allow to dry. Recommended for repeated use.

Warnings

For external use only: hands.

Flammable, keep away from fire or flame.

When using this product avoid contact with the eyes. In case of contact, Rinse eyes thoroughly with water.

Stop use and ask a doctor if irritation or redness appears and lasts.

If swallowed, get medical help or contact a Poison Control Center immediately.

Do not use: in children less than 2 months of age and on open wounds. Do not inhale or ingest.

Supervise children under 6 years of age when using the product to avoid swallowing.

Other information

Store between 0^0C (32^0F) – 41^0C (105^0F)

Inactive ingredients

Glycerin, Hydrogen Peroxide, Distilled Water, Polymer, Fragrance.

Customer service

1-833-SANITIZE